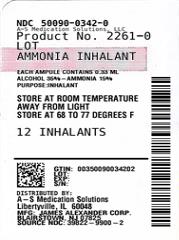 DRUG LABEL: Ammonia Inhalants
NDC: 50090-0342 | Form: INHALANT
Manufacturer: A-S Medication Solutions
Category: prescription | Type: HUMAN PRESCRIPTION DRUG LABEL
Date: 20210414

ACTIVE INGREDIENTS: AMMONIA 0.045 g/0.3 mL
INACTIVE INGREDIENTS: ALCOHOL; FD&C RED NO. 40; LAVENDER OIL; WATER; NUTMEG OIL; LEMON OIL

Ammonia Inhalants

Active ingredient(s)

Ammonia (15%)

Purpose

Inhalant

Use(s)

To prevent or treat fainting

Warnings

Keep away from the Eyes.

Stop use and ask a doctor if

condition persists

Keep out of reach of children

If swallowed, get medical help or contact a Poison Control Center right away.

Directions

Directions: hold inhalant away from face and crush between thumb and forefinger. Carefully approach crushed inhalant to nostrils of affected person.

Other information

Store at room temperature away from light.

Storage

Store at 20ºC to 25ºC (68ºF to 77ºF)

Inactive ingredients

Alcohol USP, FDC red dye 40, lavender oil fcc, lemon oil fcc, nutmeg oil fcc, purified water usp

Questions

Questions? Call 1-866-390-4411 Mon - Fri 9:00 AM - 5:00 PM